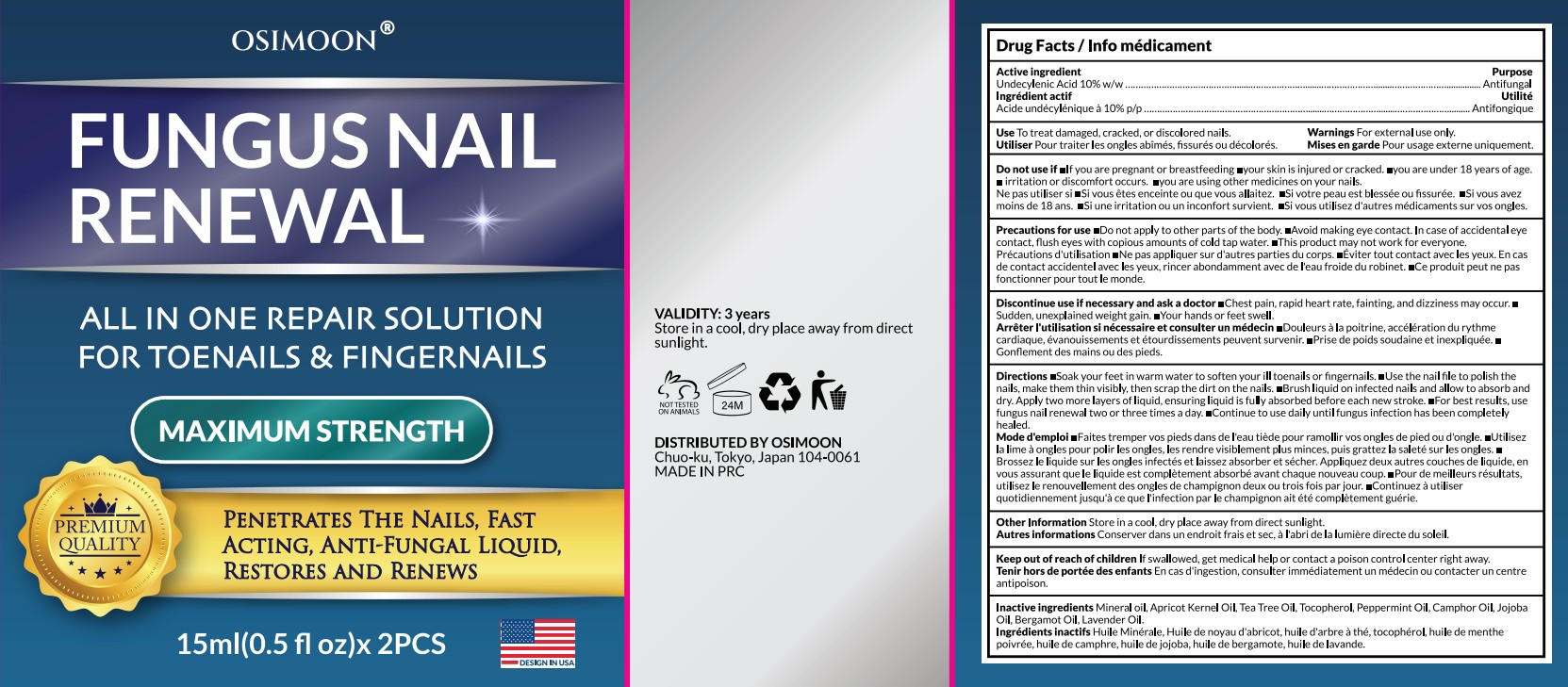 DRUG LABEL: OSIMOON FUNGAL NAIL RENEWAL
NDC: 87408-006 | Form: LIQUID
Manufacturer: Guangzhou Jingliang Cosmetics Co., Ltd.
Category: otc | Type: HUMAN OTC DRUG LABEL
Date: 20260217

ACTIVE INGREDIENTS: UNDECYLENIC ACID 10 g/100 mL
INACTIVE INGREDIENTS: PEPPERMINT OIL; CAMPHOR OIL; JOJOBA OIL; APRICOT KERNEL OIL; MINERAL OIL; LAVENDER OIL; BERGAMOT OIL; TOCOPHEROL; TEA TREE OIL

Active Ingredient

Active ingredient: Undecylenic Acid 10%

Ask Doctor

if irritation or symptoms worsen or last for more than 4 weeks.

Do not use

• If you are pregnant or breastfeeding
• your skin is injured or cracked.
• you are under 18 years of age.
• irritation or discomfort occurs.
• you are using other medicines on your nails.

Keep Oot Of Reach Of Children

If swallowed, get medical help or contact a poison control center right away.

Purpose

Antifungal

Stop Use

Discontinue use if necessary and ask a doctor:

Chest pain, rapid heart rate, fainting, and dizziness may occur.

Sudden, unexplained weight gain.

Your hands or feet swell.

When Using

• Do not apply to other parts of the body.
• Avoid making eye contact. In case of accidental eye contact, flush eyes with copious amounts of cold tap water.
• This product may not work for everyone.

Inactive ingredients

Mineral oil, Apricot Kernel Oil, Tea Tree Oil,Tocopherol, Peppermint Oil, Camphor Oil, Jojoba Oil, Bergamot Oil, Lavender Oil

Directions

Soak your feet in warm water to soften your toenails or fingernails.

Use the nail file to polish the nails, make them thin visibly, then scrap the dirt on the nails.

Brush liquid on infected nails and allow to absorb and dry.

Apply two more layers of liquid, ensuring liquid is fully absorbed before each new stroke.

For best results, use fungus nail renewal two or three times a day.

Continue to use daily until fungus infection has been completely healed.

Warnings

• For external use only.
• When using this product avoid contact with eyes. If contact occurs, rinse thoroughly with water.
• Stop use and ask/ consult a doctor/ physician/ health care practitioner/ health care provider/ health care professional if irritation or symptoms worsen or last for more than 4 weeks.
• Keep out of reach of children. If swallowed, call a poison control centre or get medical help right away.

Uses

To treat damaged, cracked, or discolored nails.

PACKAGE LABEL

Product Name: OSIMOON FUNGAL NAIL RENEWAL

Net Contents: 2x15ml (0.5 fl.oz.) Bottles